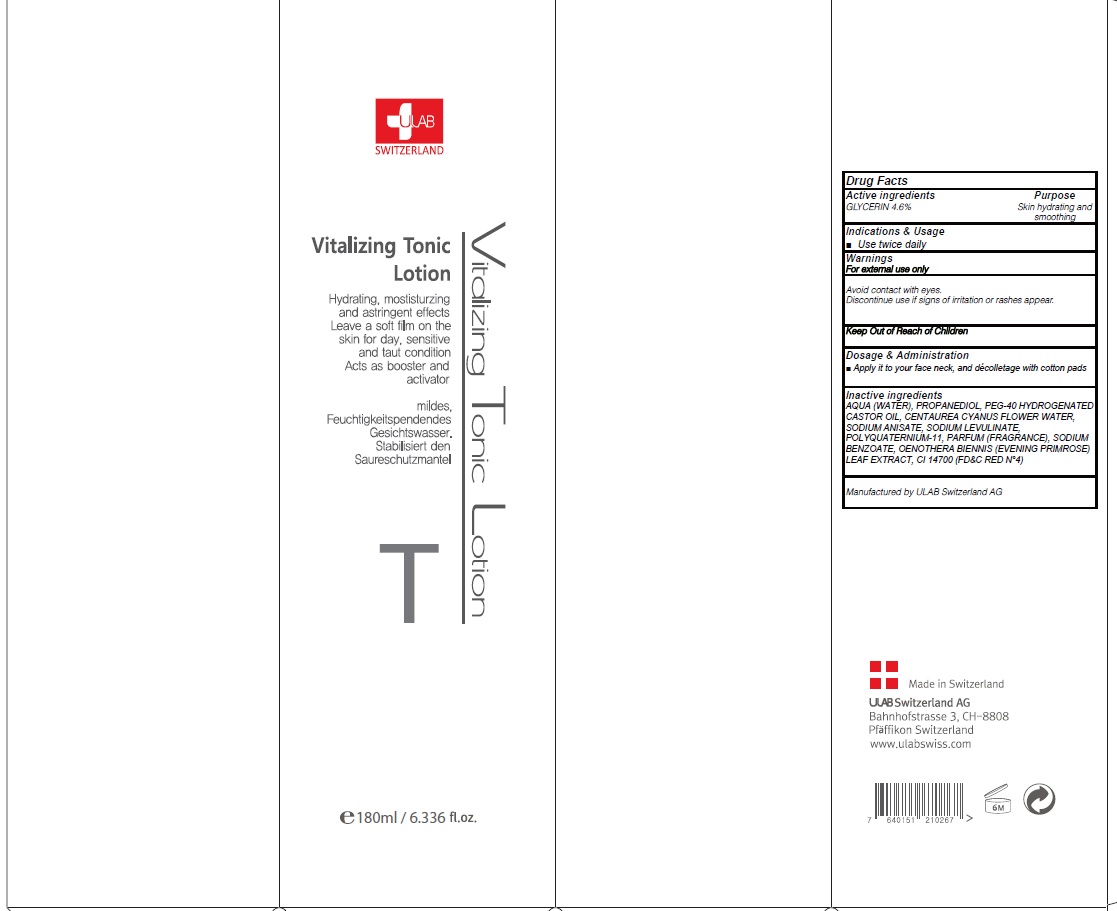 DRUG LABEL: VITALISING TONIC
NDC: 71276-010 | Form: LOTION
Manufacturer: ULAB
Category: otc | Type: HUMAN OTC DRUG LABEL
Date: 20170321

ACTIVE INGREDIENTS: GLYCERIN 8.28 g/180 mL
INACTIVE INGREDIENTS: WATER; PROPANEDIOL

ACTIVE INGREDIENT

Active ingredients: GLYCERIN 4.6%

INACTIVE INGREDIENT

Inactive ingredients: AQUA (WATER), PROPANEDIOL, PEG-40 HYDROGENATED CASTOR OIL, CENTAUREA CYANUS FLOWER WATER, SODIUM ANISATE, SODIUM LEVULINATE, POLYQUATERNIUM-11, PARFUM (FRAGRANCE), SODIUM BENZOATE, OENOTHERA BIENNIS (EVENING PRIMROSE) LEAF EXTRACT, CI 14700 (FD&C RED N°4)

PURPOSE

Purpose: Skin hydrating and smoothing

WARNINGS

Warnings: For external use only Avoid contact with eyes. Discontinue use if signs of irritation or rashes appear.

KEEP OUT OF REACH OF CHILDREN

INDICATIONS & USAGE

Indications & Usage: Use twice daily

DOSAGE & ADMINISTRATION

Dosage & Administration: Apply it to your face neck, and decolletage with cotton pads